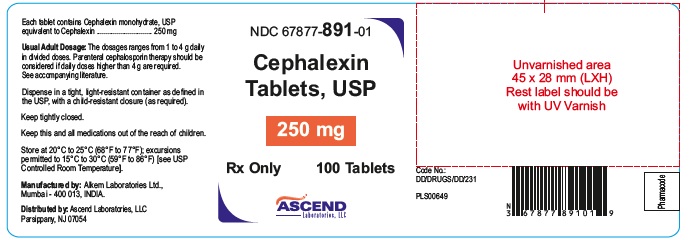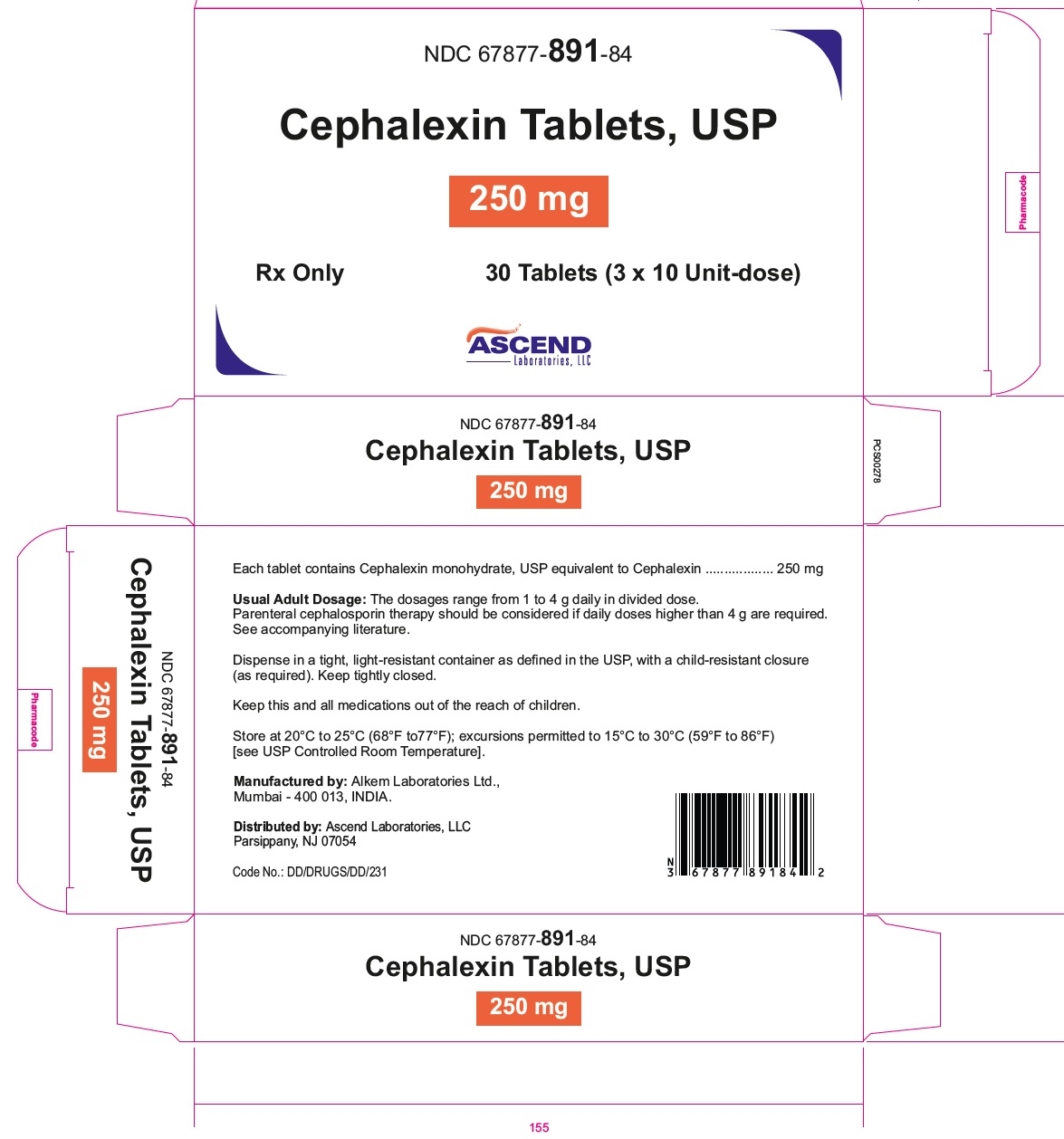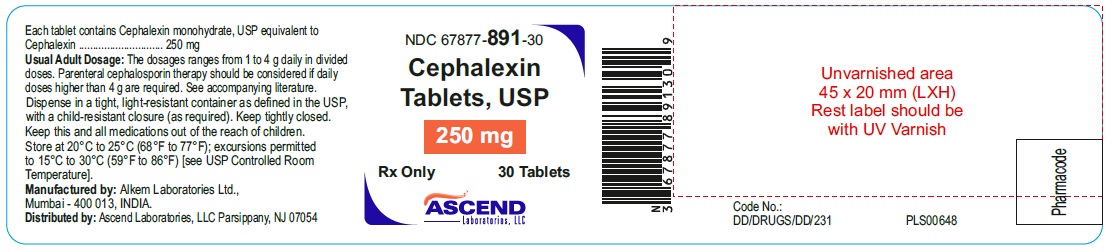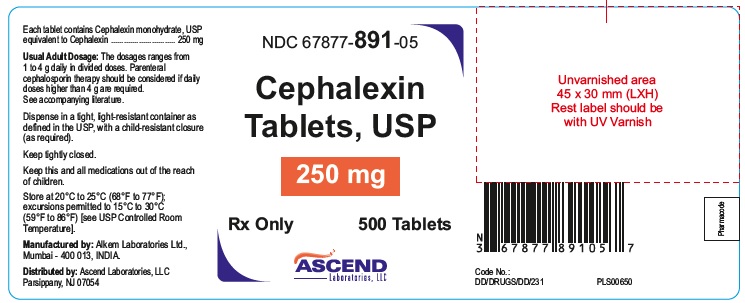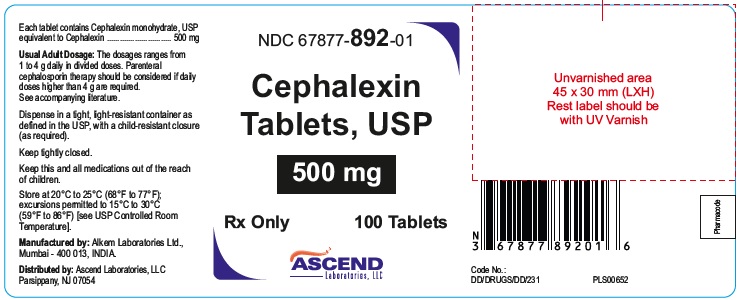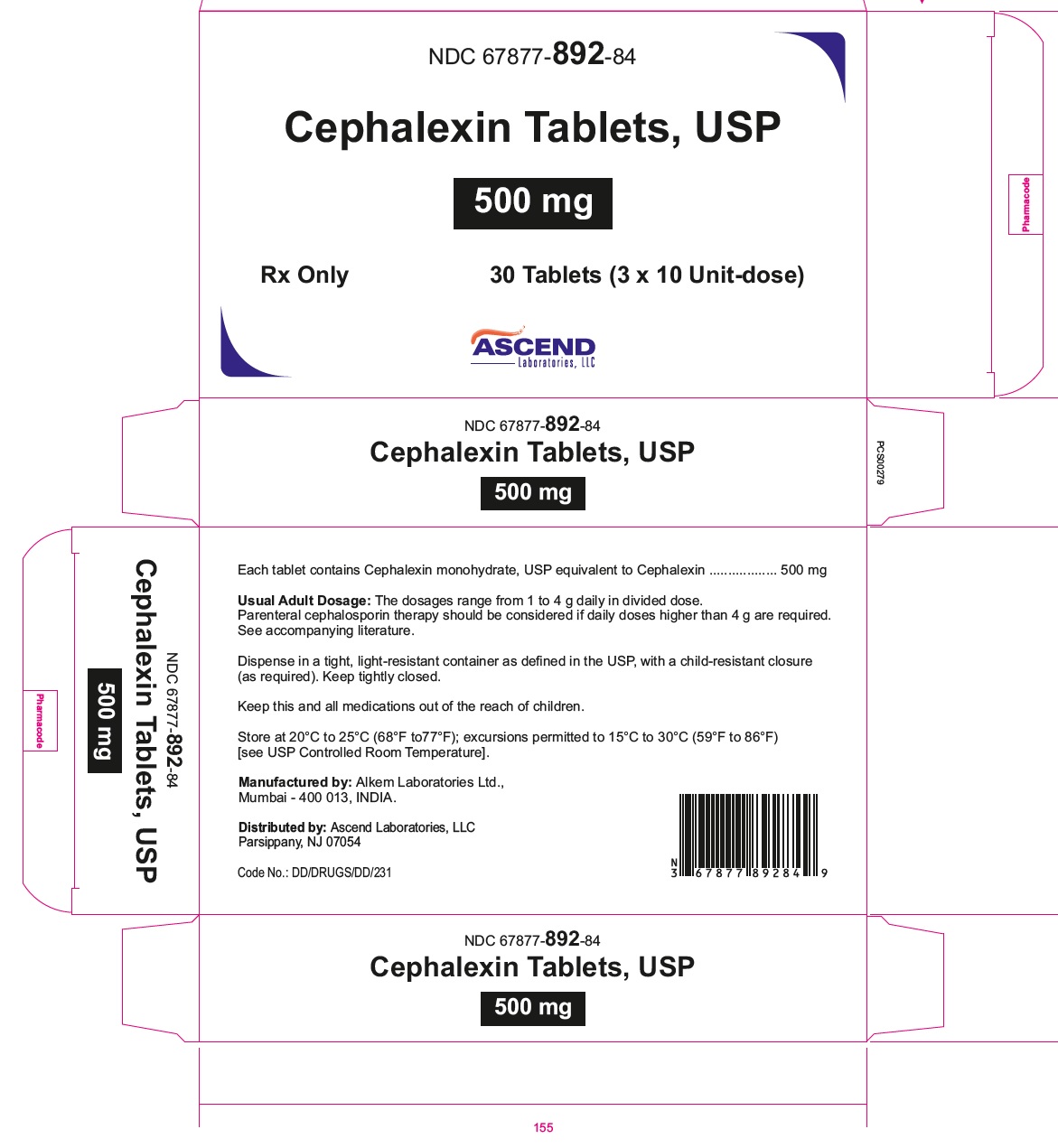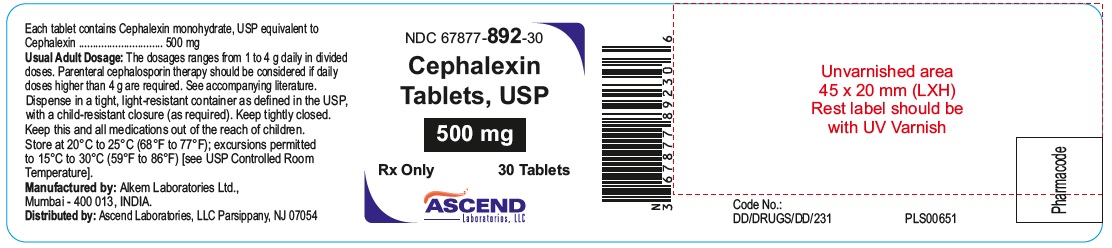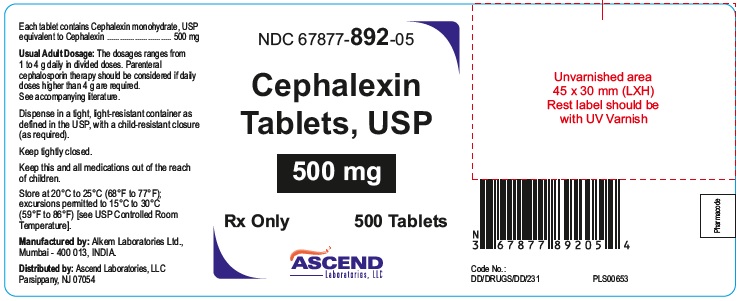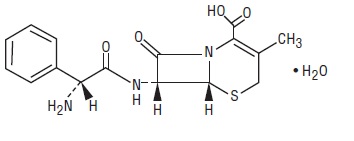 DRUG LABEL: Cephalexin
NDC: 67877-891 | Form: TABLET
Manufacturer: Ascend Laboratories, LLC
Category: prescription | Type: Human Prescription Drug Label
Date: 20241018

ACTIVE INGREDIENTS: CEPHALEXIN 250 mg/1 1
INACTIVE INGREDIENTS: HYPROMELLOSE, UNSPECIFIED; HYDROXYPROPYL CELLULOSE, UNSPECIFIED; MAGNESIUM STEARATE; MICROCRYSTALLINE CELLULOSE; SILICON DIOXIDE; SODIUM STARCH GLYCOLATE TYPE A; TALC; TITANIUM DIOXIDE; HYDROXYPROPYL CELLULOSE, LOW SUBSTITUTED

Cephalexin Tablets, USP
To reduce the development of drug-resistant bacteria and maintain the effectiveness of cephalexin tablets and other antibacterial drugs, cephalexin tablets should be used only to treat or prevent infections that are proven or strongly suspected to be caused by bacteria.

DESCRIPTION

Cephalexin tablets, USP contain the active ingredient cephalexin, which is a semisynthetic cephalosporin antibiotic intended for oral administration. It is 7-(D-α-amino-α-phenylacetamido)-3-methyl-3-cephem-4-carboxylic acid, monohydrate.

Cephalexin has the molecular formula C16H17N3O4S•H2O and the molecular weight is 365.41.

Cephalexin has the following structural formula:

The nucleus of cephalexin is related to that of other cephalosporin antibiotics. The compound is a zwitterion; i.e., the molecule contains both a basic and an acidic group. The isoelectric point of cephalexin in water is approximately 4.5 to 5.

The crystalline form of cephalexin which is available is a monohydrate. It is a white to off white crystalline powder. Slightly soluble in water, practically insoluble alcohol, in chloroform and in ether.

The cephalosporins differ from penicillins in the structure of the bicyclic ring system. Cephalexin has a D-phenylglycyl group as substituent at the 7-amino position and an unsubstituted methyl group at the 3-position.

Each tablet contains cephalexin monohydrate equivalent to 250 mg or 500 mg of cephalexin. The tablets also contain the inactive ingredients: hypromellose, hydroxypropyl cellulose, low-substituted hydroxypropyl cellulose, magnesium stearate, microcrystalline cellulose, silicon dioxide, sodium starch glycolate, talc and titanium dioxide.

FDA approved dissolution test specifications differ from USP

CLINICAL PHARMACOLOGY

Human Pharmacology

Cephalexin tablets are acid stable and may be given without regard to meals. It is rapidly absorbed after oral administration. Following doses of 250 mg, 500 mg, and 1g, average peak serum levels of approximately 9, 18, and 32 mcg/mL, respectively, were obtained at 1 hour. Serum levels were detectable 6 hours after administration (at a level of detection of 0.2 mcg/mL). Cephalexin is approximately 10% to 15% bound to plasma proteins. Cephalexin is excreted in the urine by glomerular filtration and tubular secretion. Studies showed that over 90% of the drug was excreted unchanged in the urine within 8 hours. During this period, peak urine concentrations following the 250-mg, 500-mg, and 1-g doses were approximately 1000, 2200, and 5000 mcg/mL, respectively.

In healthy subjects given single 500 mg doses of cephalexin and metformin, plasma metformin mean Cmax and AUC increased by an average of 34% and 24%, respectively, and metformin mean renal clearance decreased by 14%. No information is available about the interaction of cephalexin and metformin following multiple doses of either drug.

Microbiology

Cephalexin is a bactericidal agent that acts by the inhibition of cell-wall synthesis.

Resistance-Methicillin-resistant staphylococci and most isolates of enterococci are resistant to cephalexin. Cephalexin is not active against most isolates of Enterobacter spp., Morganella morganii, and Proteus vulqaris. Cephalexin has no activity against Pseudomonas spp., or Acinetobacter calcoaceticus. Penicillinresistant Streptococcus pneumoniae is usually cross-resistant to beta-lactam

antibacterial drugs.

Antimicrobial Activity - Cephalexin is active against most isolates of the following bacteria both in vitro and in clinical infections [see INDICATIONS and USAGE]:

Gram-positive bacteria

Staphylococci aureus (methicillin-susceptible isolates only),

Streptococcus pneumoniae (penicillin-susceptible isolates)

Streptococcus pyogenes

Gram-negative bacteria

Escherichia coli

Haemophilus influenzae

Klebsiella pneumoniae

Moraxella catarrhalis

Proteus mirabilis

Susceptibility Testing-

For specific information regarding susceptibility test interpretive criteria and associated test methods and quality control standards recognized by FDA for this drug, please see: https://www.fda.gov/STIC.

INDICATIONS & USAGE

Cephalexin tablets are indicated for the treatment of the following infections when caused by susceptible strains of the designated microorganisms:

Respiratory tract infections caused by susceptible isolates of Streptococcus pneumoniae and Streptococcus pyogenes

Otitis media due to susceptible isolates of Streptococcu.. pneumoniae, Haemophilus influenzae, Staphylococcus aureus, Streptococcus pyogenes, and Moraxella Catarrhalis.

Skin and skin structure infections caused by susceptible isolates of the following Gram-positive bacteria: Staphylococcus aureus, and Streptococcus pyogenes

Bone infections caused by susceptible isolates of Staphylococcus aureus and Proteus Mirabilis

Genitourinary tract infections, including acute prostatitis, caused by susceptible isolates of Escherichia coli, Proteus mirabilis, and Klebsiella pneumoniare

To reduce the development of drug-resistant bacteria and maintain the effectiveness of cephalexin tablets and other antibacterial drugs, cephalexin tablets should be used only to treat or prevent infections that are proven or strongly suspected to be caused by susceptible bacteria. When culture and susceptibility information are available, they should be considered in selecting or modifying antibacterial therapy. In the absence of such data, local epidemiology and susceptibility patterns may contribute to the empiric selection of therapy.

CONTRAINDICATION

Cephalexin tablets are contraindicated in patients with known allergy to cephalexin or other members of the cephalosporin class of antibacterial drugs.

WARNINGS

Hypersensitivity Reactions

Allergic reactions in the form of rash, urticaria, angioedema, anaphylaxis, erythema multiforme, Stevens-Johnson syndrome, or toxic epidermal necrolysis have been reported with the use of cephalexin tablets. Before therapy with cephalexin tablets are instituted, inquire whether the patient has a history of hypersensitivity reactions to cephalexin, cephalosporins, penicillins, or other drugs. Cross-hypersensitivity among beta-lactam antibacterial drugs may occur in up to 10% of patients with a history of penicillin allergy.

If an allergic reaction to cephalexin tablets occurs, discontinue the drug and institute appropriate treatment.

Clostridium difficile-Associated Diarrhea

Clostridium difficile-associated diarrhea (CDAD)has been reported with use of nearly all antibacterial agents, including cephalexin tablets, and may range in severity from mild diarrhea to fatal colitis. Treatment with antibacterial agents alters the normal flora of the colon leading to overgrowth of C. difficile.

C. difficile produces toxins A and B, which contribute to the development of CDAD. Hypertoxin-producing strains of C. difficile cause increased morbidity and mortality, as these infections can be refractory to antimicrobial therapy and may require colectomy. CDAD must be considered in all patients who present with diarrhea following antibiotic use. Careful medical history is necessary since CDAD has been reported to occur over two months after the administration of antibacterial agents.

If CDAD is suspected or confirmed, ongoing antibiotic use not directed against C. difficile may need to be discontinued. Appropriate fluid and electrolyte management, protein supplementation, antibiotic treatment of C. difficile, and surgical evaluation should be instituted as clinically indicated

Direct Coomb’s Test Seroconversion

Positive direct Coombs tests have been reported during treatment with the cephalosporin antibacterial drugs including cephalexin. Acute intravascular hemolysis induced by cephalexin therapy has been reported. If anemia develops during or after cephalexin therapy, perform a diagnostic work-up for drug-induced hemolytic anemia, discontinue cephalexin and institute appropriate therapy.

Seizure Potential

Several cephalosporins have been implicated in triggering seizures, particularly in patients with renal impairment when the dosage was not reduced. If seizures occur, discontinue cephalexin tablets. Anticonvulsant therapy can be given if clinically indicated.

Prolonged Prothrombin Time

Cephalosporins may be associated with prolonged prothrombin time. Those at risk include patients with renal or hepatic impairment, or poor nutritional state, as well as patients receiving a protracted course of antibacterial therapy, and patients receiving anticoagulant therapy. Monitor prothrombin time in patients at risk and manage as indicated.

PRECAUTIONS

GENERAL

Prescribing cephalexin tablets in the absence of a proven or strongly suspected bacterial infection or a prophylactic indication is unlikely to provide benefit to the patient and increases the risk of the development of drug-resistant bacteria.

Prolonged use of cephalexin tablets may result in the overgrowth of nonsusceptible organisms. Careful observation of the patient is essential. If superinfection occurs during therapy, appropriate measures should be taken.

INFORMATION FOR PATIENTS

Advise patients that allergic reactions, including serious allergic reactions, could occur and that serious reactions require immediate treatment. Ask the patient about any previous hypersensitivity reactions to cephalexin tablets, other beta-lactams (including cephalosporins) or other allergens [see WARNINGS].

Diarrhea is a common problem caused by antibiotics which usually ends when the antibiotic is discontinued. Sometimes after starting treatment with antibiotics, patients can develop watery and bloody stools (with or without stomach cramps and fever) even as late as two or more months after having taken the last dose of the antibiotic. If this occurs, patients should contact their physician as soon as possible.

Patients should be counseled that antibacterial drugs including cephalexin tablets should only be used to treat bacterial infections. They do not treat viral infections (e.g., the common cold). When cephalexin tablets are prescribed to treat a bacterial infection, patients should be told that although it is common to feel better early in the course of therapy, the medication should be taken exactly as directed. Skipping doses or not completing the full course of therapy may (1) decrease the effectiveness of the immediate treatment and (2) increase the likelihood that bacteria will develop resistance and will not be treatable by cephalexin tablets or other antibacterial drugs in the future.

DRUG INTERACTIONS

Metformin: Administration of cephalexin tablets with metformin results in increased plasma metformin concentrations and decreased renal clearance of metformin. Careful patient monitoring and dose adjustment of metformin is recommended in patients concomitantly taking cephalexin tablets and metformin[see CLINICAL PHARMACOLOGY].

Probenecid:The renal excretion of cephalexin tablets is inhibited by probenecid. Co-administration of probenecid with cephalexin tablets is not recommended.

Drug/laboratory Test Interactions: A false-positive reaction may occur when testing for the presence of glucose in the urine using Benedict's solution or Fehling's solutions.

PREGNANCY

Reproduction studies have been performed on mice and rats using oral doses of cephalexin monohydrate 0.6 and 1.5 times the maximum daily human dose (66 mg/kg/day) based upon body surface area basis and have revealed no evidence of impaired fertility or harm to the fetus. There are, however, no adequate and well-controlled studies in pregnant women. Because animal reproduction studies are not always predictive of human response, this drug should be used during pregnancy only if clearly needed.

NURSING MOTHERS

Cephalexin is excreted in human milk. Caution should be exercised when cephalexin tablets are administered to a nursing woman.

PEDIATRIC USE

The safety and effectiveness of cephalexin tablets in pediatric patients was established in clinical trials for the dosages described in the dosage and administration section [see DOSAGE AND ADMINISTRATION].

GERIATRIC USE

Of the 701 subjects in 3 published clinical studies of cephalexin, 433 (62%) were 65 and over. No overall differences in safety or effectiveness were observed between these subjects and younger subjects, and other reported clinical experience has not identified differences in responses between the elderly and younger patients.

This drug is substantially excreted by the kidney, and the risk of toxic reactions to this drug may be greater in patients with impaired renal function. Because elderly patients are more likely to have decreased renal function, care should be taken in dose selection.

Renal Impairment

Cephalexin tablets should be administered with caution in the presence of impaired renal function (creatinine clearance < 30 mL/min, with or without dialysis). Under such conditions, careful clinical observation and laboratory studies should be made because safe dosage may be lower than that usually recommended [see DOSAGE AND ADMINISTRATION].

ADVERSE REACTIONS

Because clinical trials are conducted under widely varying conditions, adverse reaction rates observed in the clinical trials of a drug cannot be directly compared to rates in the clinical trials of another drug and may not reflect the rates observed in practice. The most frequent adverse reaction was diarrhea. Nausea and vomiting, dyspepsia, gastritis, and abdominal pain have also occurred. As with penicillins and other cephalosporins, transient hepatitis and cholestatic jaundice have been reported.

Other reactions have included hypersensitivity reactions, genital and anal pruritus, genital candidiasis, vaginitis and vaginal discharge, dizziness, fatigue, headache, agitation, confusion, hallucinations, arthralgia, arthritis, and joint disorder. Reversible interstitial nephritis has been reported. Eosinophilia, neutropenia, thrombocytopenia, hemolytic anemia, and slight elevations in aspartate transaminase (AST) and alanine transaminase (ALT) have been reported.

In addition to the adverse reactions listed above that have been observed in patients treated with cephalexin tablets, the following adverse reactions and other altered laboratory tests have been reported for cephalosporin class antibacterial drugs:

Other Adverse Reactions: Fever, colitis, aplastic anemia, hemorrhage, renal dysfunction, and toxic nephropathy.

Altered Laboratory Tests: Prolonged prothrombin time, increased blood urea nitrogen (BUN), increased creatinine, elevated alkaline phosphatase, elevated bilirubin, elevated lactate dehydrogenase (LDH), pancytopenia, leukopenia, and agranulocytosis.

OVERDOSAGE

Symptoms of oral overdose may include nausea, vomiting, epigastric distress, diarrhea, and hematuria. In the event of an overdose, institute general supportive measures.

Forced diuresis, peritoneal dialysis, hemodialysis, or charcoal hemoperfusion have not been established as beneficial for an overdose of cephalexin.

DOSAGE & ADMINISTRATION

Cephalexin tablets are administered orally.

Adults and Pediatric Patients at Least 15 Years of Age

The usual dose is 250 mg every 6 hours but a dose of 500 mg every 12 hours may be administered. Treatment is administered for 7 to 14 days. For more severe infections larger doses of oral cephalexin may be needed, up to 4 grams in two to four equally divided doses.

Pediatric Patients (over 1 year of age)

The recommended total daily dose of oral cephalexin for pediatric patients is 25 to 50 mg/kg in equally divided doses for 7 to 14 days. In the treatment of β-hemolytic streptococcal infections, duration of at least 10 days is recommended. In severe infections, a total daily dose of 50 to 100 mg/kg may be administered

in equally divided doses.

In the treatment of otitis media, the recommended daily dose is 75 to 100 mg/kg/day in equally divided doses.

Dosage adjustments in Adults and Pediatric Patients at Least 15 years of

Age with Renal Impairment

Administer the following dosing regimens for cephalexin tablets to patients with renal impairment [see PRECAUTIONS].

Table 1. Recommended Dose Regimen for Patients with Renal Impairment

Renal function | Dose regimen recommendation
Creatinine clearance >60 mL/min | No dose adjustment
Creatinine clearance 30 to 59 mL/min | No dose adjustment; maximum daily dose should not exceed 1 g
Creatinine clearance 15 to 29 mL/min | 250 mg, every 8 hours or every 12 hours
Creatinine clearance 5 to 14 mL/min not yet on dialysis* | 250 mg, every 24 hours
Creatinine clearance 1 to 4 mL/min not yet on dialysis* | 250 mg, every 48 hours or every 60 hours

*There is insufficient information to make dose adjustment recommendations in patients on hemodialysis.

HOW SUPPLIED

Cephalexin tablets USP—

250 mg: white to off white, capsule-shaped coated tablet, debossed “250” on one side with score between the “2” and “5” and “CEP” on the reverse side. They are available as follows:

Bottles of 30 NDC 67877-891-30

Bottles of 100 NDC 67877-891-01

Bottles of 500 NDC 67877-891-05

Carton of 30 Tablets (3 x 10 Unit-dose) NDC 67877-891-84

500 mg: white to off white, capsule-shaped coated tablet, debossed “500” on one side with score between the “5” and “0” and “CEP” on the reverse side.

Bottles of 30 NDC 67877-892-30

Bottles of 100 NDC 67877-892-01

Bottles of 500 NDC 67877-892-05

Carton of 30 Tablets (3 x 10 Unit-dose) NDC 67877-892-84

Store at 20°C to 25°C (68°F to77°F); excursions permitted to 15°C to 30°C (59°F to 86°F) [see USP Controlled Room Temperature].

Manufactured by:

Alkem Laboratories Ltd.,
Mumbai - 400 013, INDIA.

Distributed by:

Ascend Laboratories, LLC

Parsippany, NJ 07054

Revised: 5/2024

PT9166

PACKAGE LABEL.PRINCIPAL DISPLAY PANEL

Cephalexin Tablets, USP 250 mg

NDC 67877-891-30
30 Tablets Container Pack
Rx Only

Cephalexin Tablets, USP 250 mg

NDC 67877-891-01
100 Tablets Container Pack
Rx Only

Cephalexin Tablets, USP 250 mg

NDC 67877-891-05
500 Tablets Container Pack
Rx Only

Cephalexin Tablets, USP 250 mg

NDC 67877-891-84
30 Tablets Carton Pack
Rx Only

Cephalexin Tablets, USP 500 mg
NDC 67877-892-30
30 Tablets Container Pack
Rx Only

Cephalexin Tablets, USP 500 mg
NDC 67877-892-01
100 Tablets Container Pack
Rx Only

Cephalexin Tablets, USP 500 mg
NDC 67877-892-05
500 Tablets Container Pack
Rx Only

Cephalexin Tablets, USP 500 mg

NDC 67877-892-84
30 Tablets Carton Pack
Rx Only